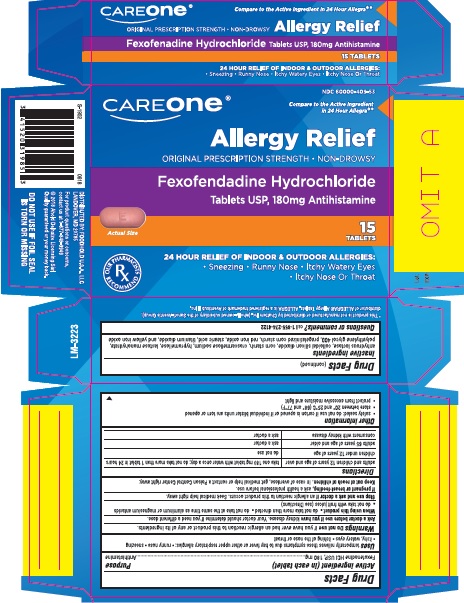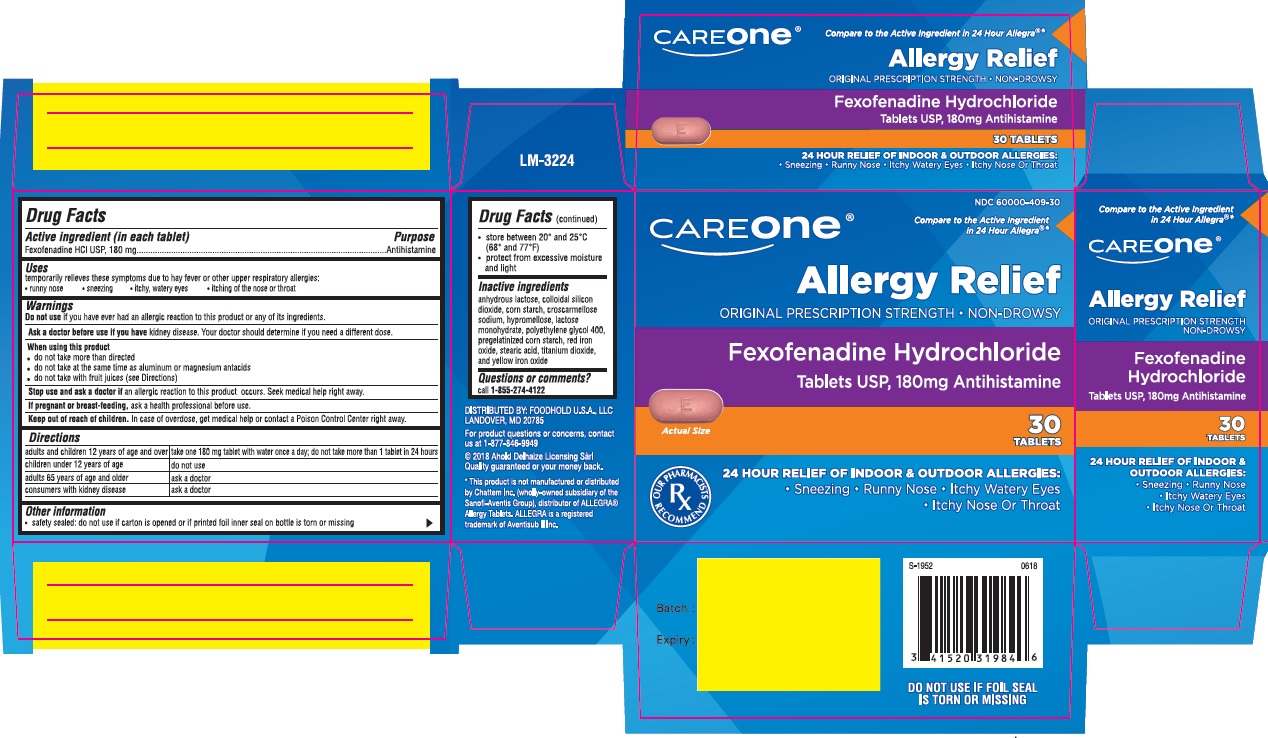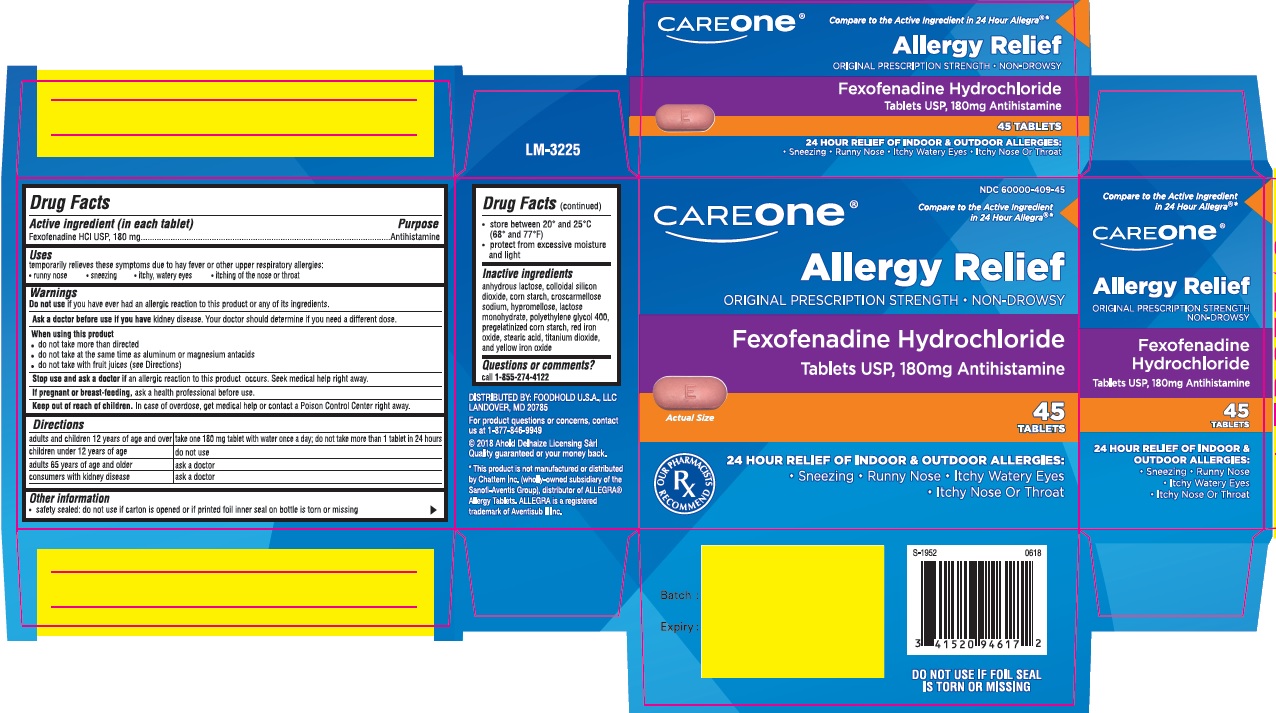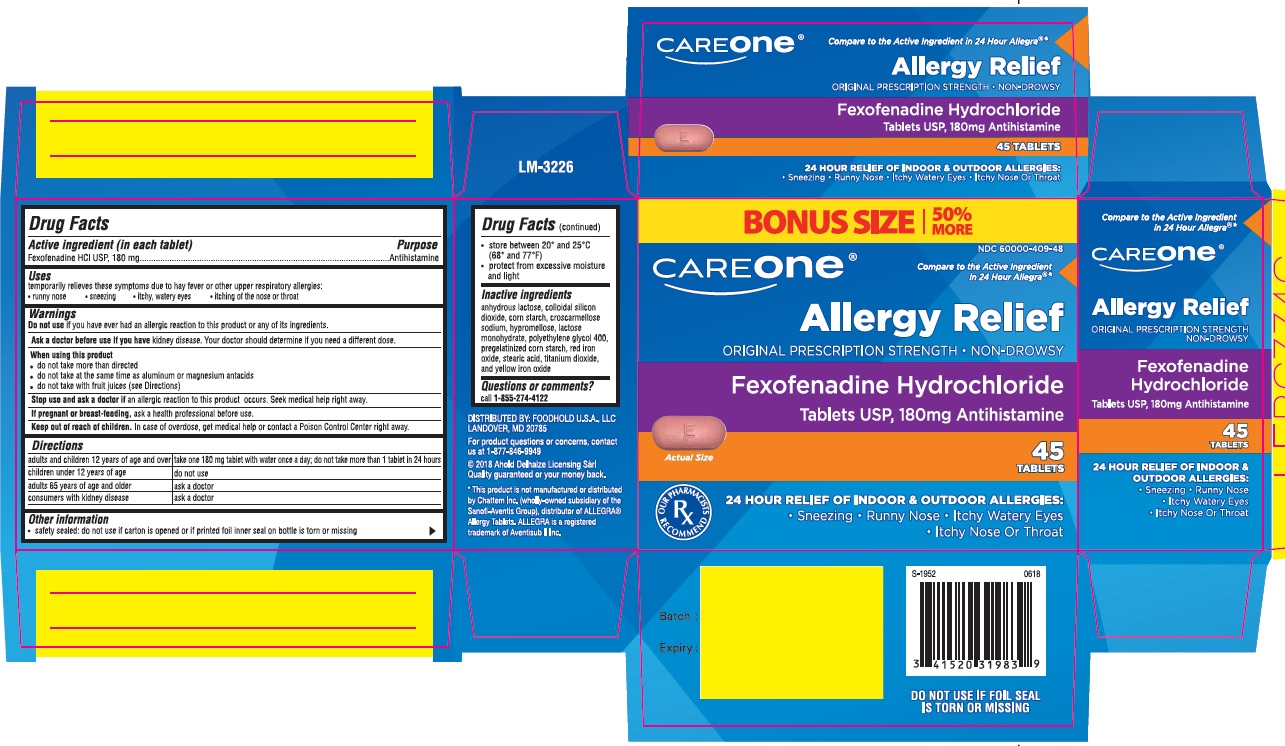 DRUG LABEL: Fexofenadine hydrochloride
NDC: 60000-409 | Form: TABLET, FILM COATED
Manufacturer: Ahold U.S.A., Inc
Category: otc | Type: Human OTC Drug Label
Date: 20190911

ACTIVE INGREDIENTS: FEXOFENADINE HYDROCHLORIDE 180 mg/1 1
INACTIVE INGREDIENTS: ANHYDROUS LACTOSE; SILICON DIOXIDE; CROSCARMELLOSE SODIUM; HYPROMELLOSES; LACTOSE MONOHYDRATE; STARCH, PREGELATINIZED CORN; STEARIC ACID; FERRIC OXIDE RED; FERRIC OXIDE YELLOW; POLYETHYLENE GLYCOL 400; TITANIUM DIOXIDE

Active ingredient(in each tablet)

Fexofenadine HCl USP, 180 mg

Purpose

Antihistamine

Uses

temporarily relieves these symptoms due to hay fever or other upper resporatory allergies:

- runny nose
- sneezing
- itchy, watery eyes
- itching of the nose or throat

Do not use

if you have ever had an allergic reaction to this product or any of its ingredients

Ask a doctor before use if you have

kidney disease. Your doctor should determine if you need a different dose.

When using this product

- do not take more than directed
- do not take at the same time as aluminium or magnesium antacids
- do not take with fruit juices (see directions)

Stop use and ask doctor if

an allergic reaction to this product occurs. Seek medical help right away.

If pregnant or breast-feeding

ask a health professional before use.

Keep out of reach of children

In case of overdose, get medical help or contact a Poison Control Center right away.

Directions

adults and children 12 years of age and over | take one 180 mg tablet with water once a day; do not take more than 1 tablet in 24 hours
children under 12 years of age | do not use
adults 65 years of age and older | ask a doctor
consumers with kidney disease | ask a doctor

Other information

- safety sealed: do not use if carton is opened or if printed foil inner seal on bottle is torn or missing
- store between 20°and 25°C (68°and 77°F)
- protect from excessive moisture and light

Inactive ingredients

anhydrous lactose, colloidal silicon dioxide, corn starch,croscarmellose sodium, hypromellose, lactose monohydrate, polyethylene glycol 400, pregelatinized corn starch, red iron oxide, steric acid, titanium dioxide, and yellow iron oxide,

Questions or comments?

call 1-855-274-4122

Principal Display Panel (180 mg 15 ct)

NDC 60000-409-53
*Compare to Active Ingredient in 24 Hour Allegra®
Original Prescription Strength Non-Drowsy
Fexofenadine Hydrochloride Tablets USP, 180 mg antihistamine
24 hour relief of Indoor & Outdoor Allergies:
Sneezing
Runny nose
Itchy, Watery Eyes
Itchy Nose or Throat

Principal Display Panel (180 mg 30 ct)

NDC 60000-409-30
*Compare to Active Ingredient in 24 Hour Allegra®
Original Prescription Strength Non-Drowsy
Fexofenadine Hydrochloride Tablets USP, 180 mg antihistamine
24 hour relief of Indoor & Outdoor Allergies:
Sneezing
Runny nose
Itchy, Watery Eyes
Itchy Nose or Throat

Principal Display Panel (180 mg 45 ct)

NDC 60000-409-45
*Compare to Active Ingredient in 24 Hour Allegra®
Original Prescription Strength Non-Drowsy
Fexofenadine Hydrochloride Tablets USP, 180 mg antihistamine
24 hour relief of Indoor & Outdoor Allergies:
Sneezing
Runny nose
Itchy, Watery Eyes
Itchy Nose or Throat

Principal Display Panel (180 mg 45 ct+ 50% bonus)

NDC 60000-409-48
*Compare to Active Ingredient in 24 Hour Allegra®
Original Prescription Strength Non-Drowsy
Fexofenadine Hydrochloride Tablets USP, 180 mg antihistamine
24 hour relief of Indoor & Outdoor Allergies:
Sneezing
Runny nose
Itchy, Watery Eyes
Itchy Nose or Throat